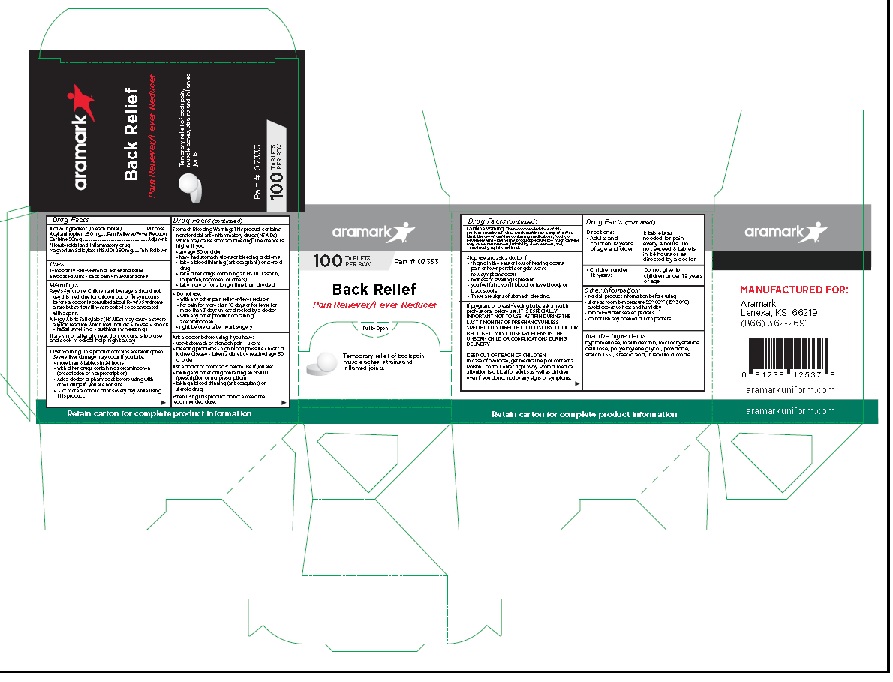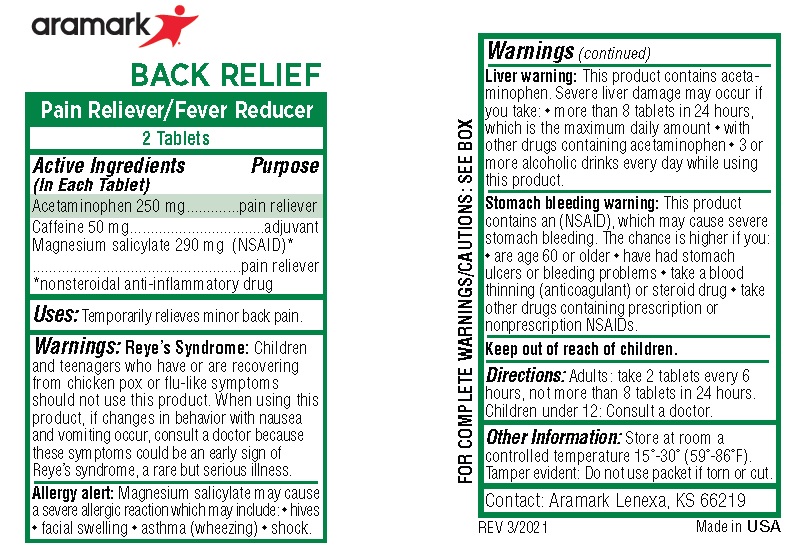 DRUG LABEL: Aramark Back Relief
NDC: 81238-1118 | Form: TABLET
Manufacturer: Western First Aid Safety DBA Aramark
Category: otc | Type: HUMAN OTC DRUG LABEL
Date: 20210624

ACTIVE INGREDIENTS: ACETAMINOPHEN 250 mg/1 1; CAFFEINE 50 mg/1 1; MAGNESIUM SALICYLATE 290 mg/1 1
INACTIVE INGREDIENTS: HYPROMELLOSE, UNSPECIFIED; MALTODEXTRIN; MICROCRYSTALLINE CELLULOSE; POLYETHYLENE GLYCOL, UNSPECIFIED; POVIDONE; STARCH, CORN; STEARIC ACID; TITANIUM DIOXIDE

Aramark Back Relief

Active Ingredient (in each tablet)
Acetaminophen 250 mg
Cafeine 50mg
*Nonsteroidal anti-inflammatory drug
Magnesium Salicylate (NSAID) 290 mg

Purpose
Acetaminophen ....Pain Reliever/Fever Reducer
Cafeine .........................................Adjuvent
*Nonsteroidal anti-inflammatory drug
Magnesium Salicylate (NSAID) ......Pain Reliever

Uses:
Temporarily Relieves minor aches and pains
associated with: • back pain • muscular aches

Warnings:

Reye’s Syndrome: Children and teenagers should not
use this medicine for chicken pox or flu symptoms
before a doctor is consulted about Reye’s Syndrome,
a rare but serious illness reported to be associated
with aspirin.

Allergy Alert: Saticylates (NSAIDs) may cause a severe
allergic reaction which may include: • hives • shock
• facial swelling • asthma (wheezing)

If a skin or allergic reaction occurs, stop use
and seek medical help right away.

Liver Warning: This product contains acetaminophen.
Severe liver damage may occur if you take:
• more than 8 tablets in 24 hours
• with other drugs containing acetaminophen
(prescription or nonprescription)
• Ask a doctor or pharmacist before using with
other drugs if you are not sure.
• 3 or more alcoholic drinks every day while using
this product.
Stomach Bleeding Warning: This product contains
nonsteroidal anti-inflammatory drugs (NSAIDs),
which may cause stomach bleeding. The chance is
higher if you:
• are age 60 or older
• have had stomach ulcers or bleeding problems
• take a blood thinning (anticoagulant) or steroid
drug
• take other drugs containing an NSAID (aspirin,
ibuprofen, naproxen, or others)
• take more or for a longer time than directed

• Do not use:
• with any other pain reliever/fever reducer
• for pain for more than 10 days or for fever for
more than 3 days unless directed by a doctor
• with any other product containing
acetaminophen
• right before or after heart surgery

Ask a doctor before using if you have:
• upset stomach or stomach pain • ulcers
• bleeding problems • high blood pressure • heart or
kidney disease • taken a diuretic • reached age 60
or older

Ask a doctor or pharmacist before use if you are:
• taking any other drug containing an NSAID
(prescription or nonprescription)
• taking a blood thinning (anticoagulant) or
steroid drug

When using this product do not exceed the
recommended dose.

Caffeine warning: The recommended dose of this
product contains about as much caffeine as a cup of coffee.
Limit the use of careline-containing medications, foods, or
beverages while taking this product because too much careline
may cause nervousness, irritability, sleeplessness, and,
occasionally, rapid heartbeat.

Stop use and ask a doctor if:
• ringing in the ears or loss of hearing occurs
• pain or fever persists or gets worse
• new symptoms occur
• redness or swelling is present
• you feel faint, vomit blood, or have bloody or
black stools.
• These are signs of stomach bleeding.

PREGNANCY OR BREAST FEEDING

If pregnant or breast-feeding baby, ask a health
professional before use. IT IS ESPECIALLY
IMPORTANT NOT TO USE ASPIRIN DURING THE
LAST 3 MONTHS OF PREGNANCY UNLESS
SPECIFICALLY DIRECTED TO DO SO BY A DOCTOR
BECAUSE IT MAY CAUSE PROBLEMS IN THE
UNBORN CHILD OR COMPLICATIONS DURING
DELIVERY.

KEEP OUT OF REACH OF CHILDREN.
In case of overdose, get medical help or contact a
Poison Control Center right away. Prompt medical
attention is critical for adults as well as children
even if you do not notice any signs or symptoms.

DOSAGE AND ADMINISTRATION

Directions: • Adults and children 12 years of age and older: | 2 tablets as needed for pain every 4 hours. Do not exceed 8 tablets in 24 hours or as directed by a doctor.
• Children under 12 years: | Do not give to children under 12 years of age

Other Information:
• read all product information before using
• store at room temperature 59°-86°F (15°-30°C)
• avoid excessive heat and humidity
• tamper-evident sealed packets
• do not use any opened or torn packets

Inactive Ingredients:
hypromellose, maltodextrin, microcrystalline
cellulose, polyethylene glycol, povidone,
starch 1551, stearic acid, titanium dioxide

Product Labeling

aramark

100 Tablets Part # 07333

Per Box

Back Relief

Pain Reliever/Fever Reducer

MANUFACTURED FOR:

Aramark
Lenexa, KS 66219
(866) 362-2691

aramarkuniform.com

Retain carton for complete product information

100 Tablet Box

2-tablet Packet